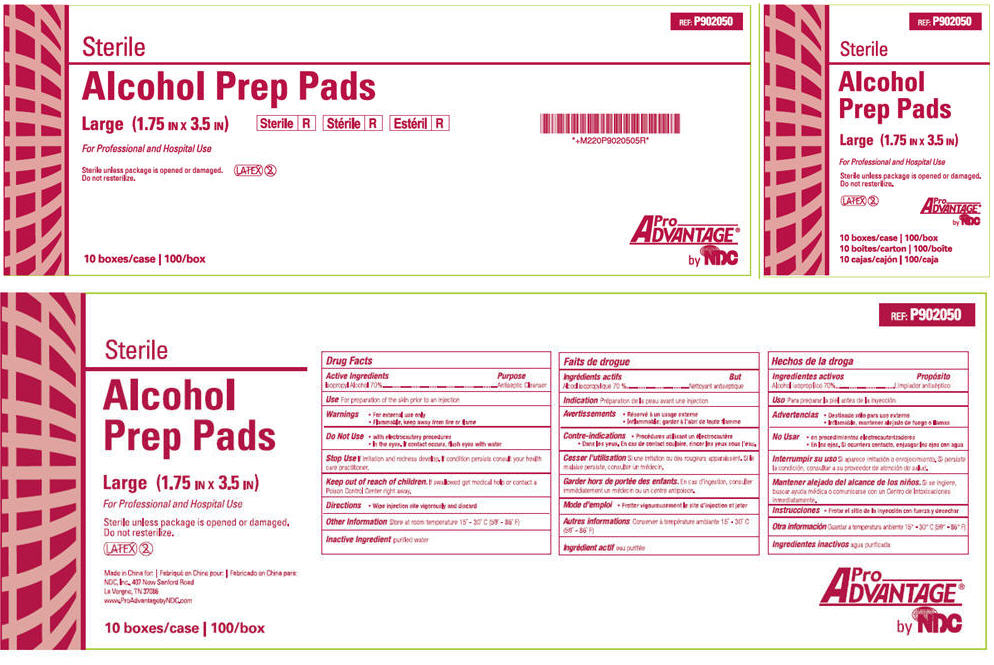 DRUG LABEL: Alcohol  Prep pad
NDC: 43128-050 | Form: SWAB
Manufacturer: NDC National Distribution & Contracting, Inc.
Category: otc | Type: HUMAN OTC DRUG LABEL
Date: 20230315

ACTIVE INGREDIENTS: ISOPROPYL ALCOHOL 0.7 mL/1 mL
INACTIVE INGREDIENTS: WATER

Sterile
Alcohol Prep Pads

Drug Facts

Active Ingredients

Isopropyl Alcohol 70%

Purpose

Antiseptic Cleanser

Use

For Preparation of Skin prior to an injection

Warnings

- For External Use Only
- Flammable, Keep away from fire or flame

Do Not Use

- with electrocautery procedures
- In the Eyes. If contact occurs, flush eyes with water

Stop Use

If irritation and redness develop. If condition persists, consult your health care practitioner.

Keep out of reach of children

If swallowed, get medical help or contact a Poison Control Center right away.

Directions

Wipe injection site vigorously and discard.

Other Information

Store at Room Temperature 15 - 30 C (59 - 86 F)

Inactive Ingredient

purified water

PRINCIPAL DISPLAY PANEL - 100 Pouch Box Label

REF: P902050

Sterile

Alcohol
Prep Pads

Large (1.75 IN × 3.5 IN)

For Professional and Hospital Use

Sterile unless package is opened or damaged.
Do not resterilize.

Pro
Advantage ®
by NDC

10 boxes/case | 100/box